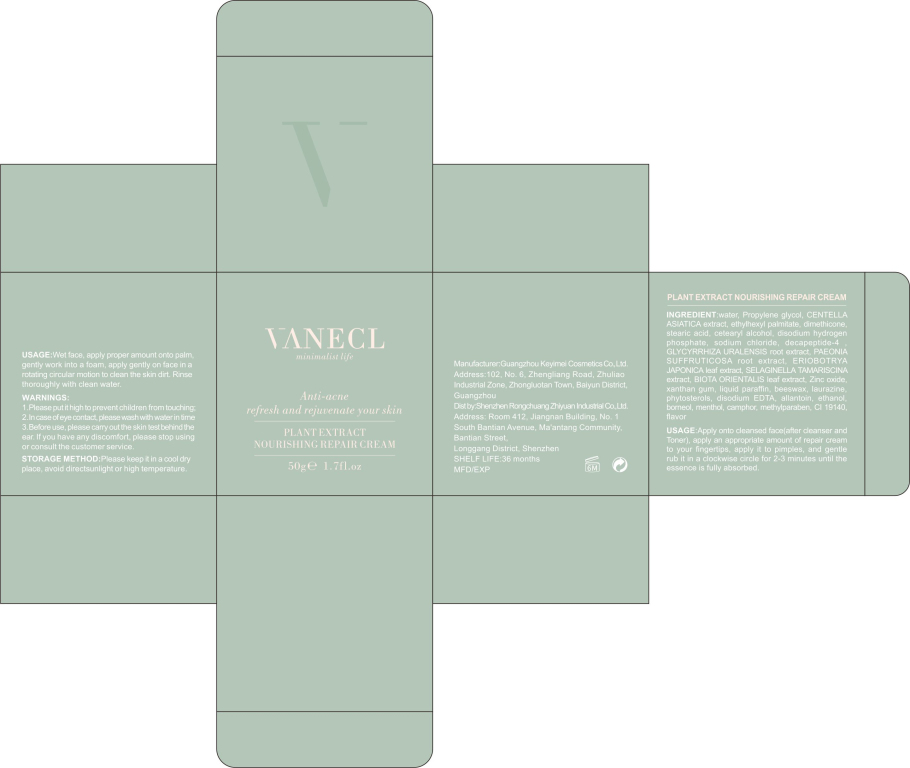 DRUG LABEL: Nursing Cream
NDC: 80377-003 | Form: CREAM
Manufacturer: Shenzhen Rongchuang Zhiyuan Industrial Co., Ltd.
Category: otc | Type: HUMAN OTC DRUG LABEL
Date: 20200903

ACTIVE INGREDIENTS: GLYCYRRHIZA URALENSIS ROOT 5 g/100 g; PAEONIA SUFFRUTICOSA ROOT 5 g/100 g; ERIOBOTRYA JAPONICA LEAF 1 g/100 g; ZINC OXIDE 2 g/100 g
INACTIVE INGREDIENTS: WATER 64.2 g/100 g

PACKAGE LABEL

50g a bottle NDC: 80377-003-01